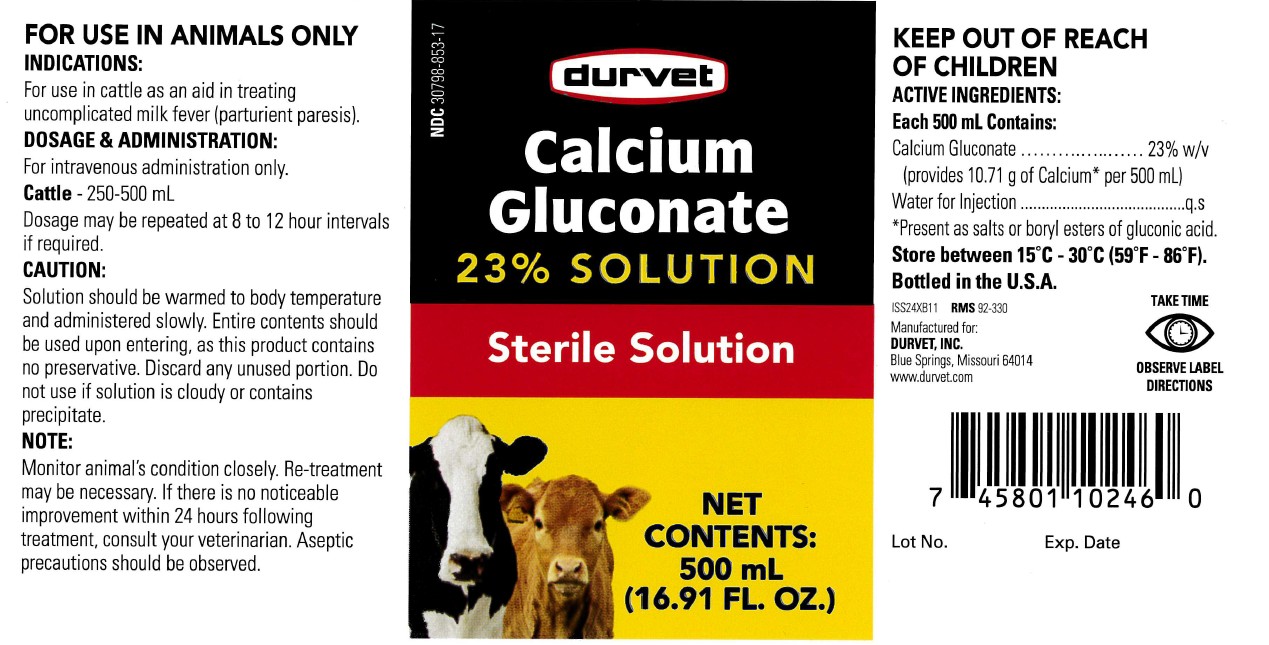 DRUG LABEL: Calcium Gluconate
NDC: 30798-853 | Form: INJECTION, SOLUTION
Manufacturer: Durvet
Category: animal | Type: OTC ANIMAL DRUG LABEL
Date: 20250728

ACTIVE INGREDIENTS: CALCIUM GLUCONATE 23 g/100 mL

CALCIUM GLUCONATE 23% SOLUTION

GENERAL PRECAUTIONS

FOR USE IN ANIMALS ONLY

ACTIVE INGREDIENTS: Each 500 mL Contains:

Calcium Gluconate.....................................23% w/v

(provides 10.71 g of Calcium* per 500 mL)

Water for Injection .....................................q.s

*Present as salts or boryl esters of gluconic acid.

INDICATIONS:

For use in cattle as an aid in treating uncomplicated milk fever (parturinet paresis).

STORAGE AND HANDLING

Store between 15°C - 30°C (59°F - 86°F).

KEEP OUT OF REACH OF CHILDREN

DOSAGE AND ADMINISTRATION:

For intravenous administration only.

Cattle - 250-500 mL

Dosage may be repeated at 8 to 12 hour intervals in required.

GENERAL PRECAUTIONS

TAKE TIME OBSERVE LABEL DIRECTIONS

INFORMATION FOR OWNERS/CAREGIVERS

NDC 30798-853-17

Sterile Solution

ISS24XB11

RMS: 92-330

Lot No. Exp. Date

NET CONTENTS:
500 mL (16.9 FL. OZ.)

Manufactured for:

DURVET, INC.
Blue Springs, MO 64014
www.durvet.com

Bottled in the U.S.A.

NOTE:

Monitor animal's condition closely. Re-treament may be necessary. If there is no noticeable improvement within 24 hours following treatment, consult your veterinarian. Aseptic precautions should be observed.